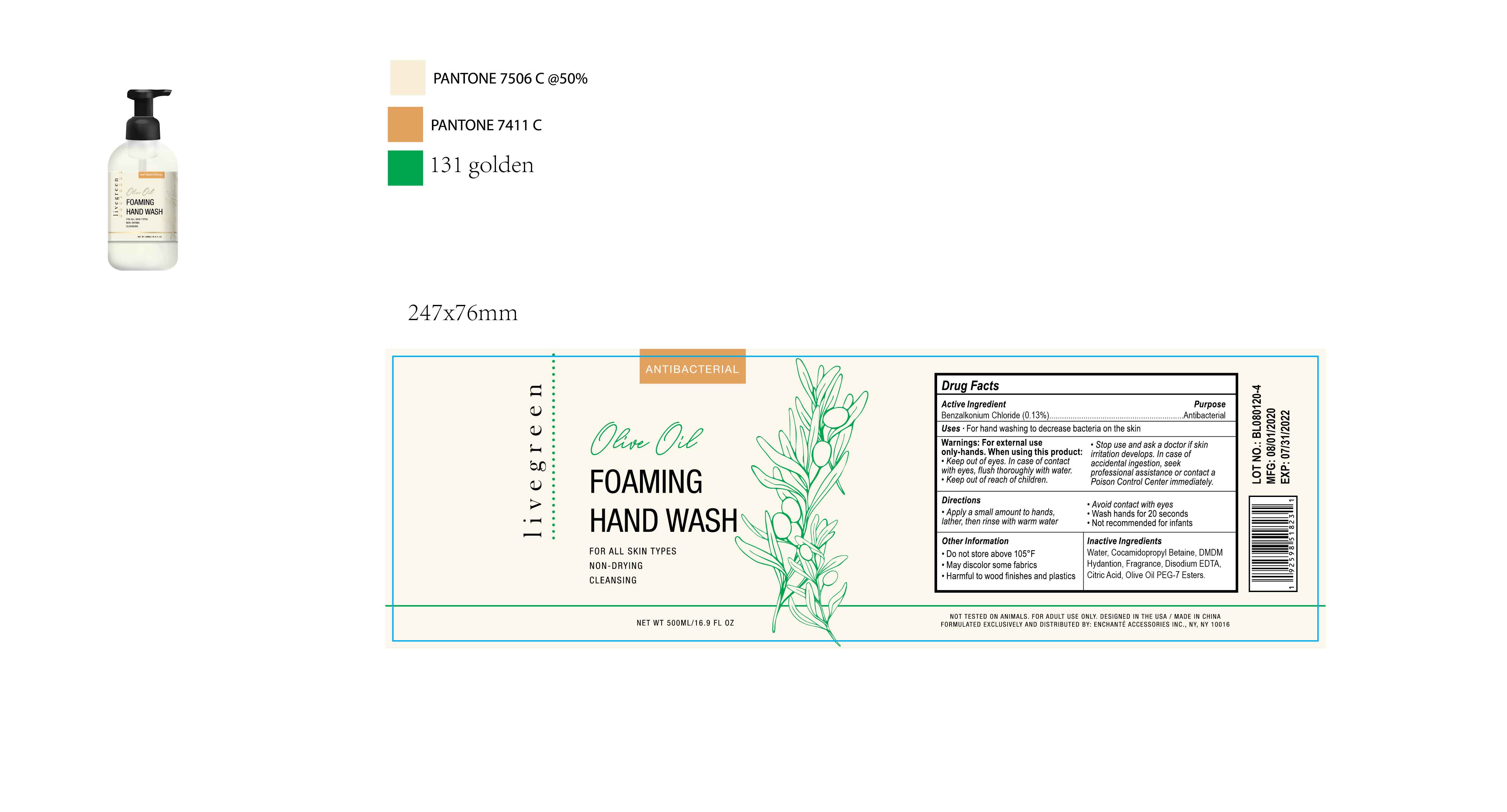 DRUG LABEL: LIVEGREEN OLIVE ANTIBACTERIAL FOAMING HAND WASH
NDC: 50563-241 | Form: SOAP
Manufacturer: ENCHANTE ACCESSORIES INC.
Category: otc | Type: HUMAN OTC DRUG LABEL
Date: 20200803

ACTIVE INGREDIENTS: BENZALKONIUM CHLORIDE 0.13 g/100 mL
INACTIVE INGREDIENTS: COCAMIDOPROPYL BETAINE; DISODIUM HEDTA; CITRIC ACID MONOHYDRATE; WATER; DMDM HYDANTOIN

G0ABHW11

Active Ingredient

Benzalkonium Chloride 0.13%

Purpose

Antibacterial

Use

■ For hand washing to decrease bacteria on the skin

WARNINGS

For external use only - hands

When Using this Product

Keep out of eyes. In case of contact with eyes, flush thoroughly with water

Stop use and ask a doctor if skin irritation develops.

Keep out of reach of children. In case of accidental ingestion, seek professional assistance or contact a poison control center immediately

Directions

Apply a small amount to hands. Lather then rinse with warm water

Avoid contact with eyes

Wash hands for 20 seconds

Not recommended for infants

Other Information

Do not store above 105F

May discolor some fabrics

Harmful to wood finishes and plastics

Inactive ingredients

Water, Cocamidopropyl Betaine, DMDM Hydantoin, Fragrance, Disodium EDTA, Citric Acid, Olive Oil PEG-7 Ester